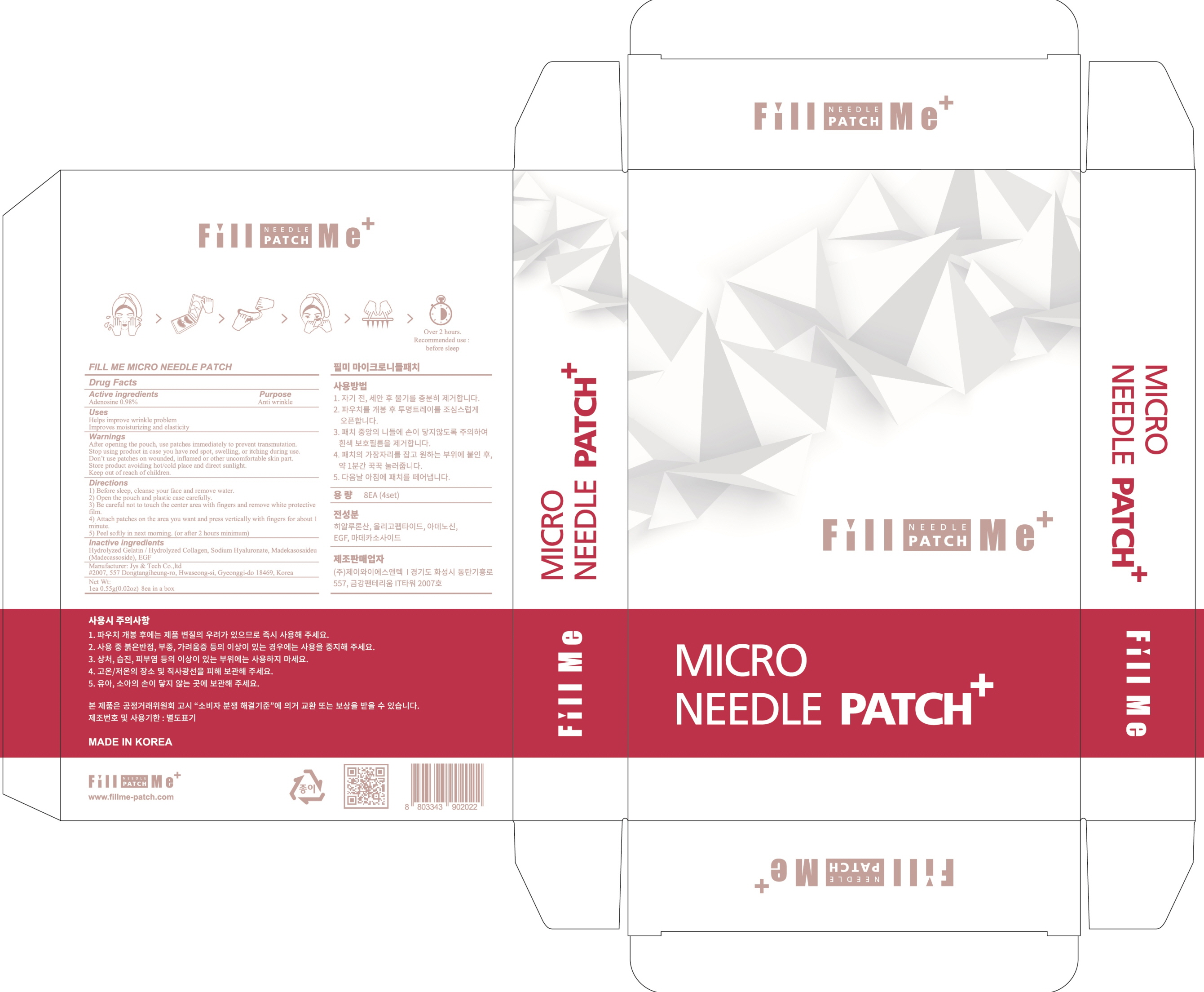 DRUG LABEL: FILL ME MICRO NEEDLE
NDC: 73312-010 | Form: PATCH
Manufacturer: Jys Tech Co.,ltd
Category: otc | Type: HUMAN OTC DRUG LABEL
Date: 20190823

ACTIVE INGREDIENTS: Adenosine 0.005 g/0.55 g
INACTIVE INGREDIENTS: Gelatin

ACTIVE INGREDIENT

Active ingredients: Adenosine 0.98%

INACTIVE INGREDIENT

Inactive ingredients:
Hydrolyzed Gelatin / Hydrolyzed Collagen, Sodium Hyaluronate, Madekasosaideu (Madecassoside), EGF

PURPOSE

Purpose: Anti wrinkle

WARNINGS

After opening the pouch, use patches immediately to prevent transmutation.
Stop using product in case you have red spot, swelling, or itching during use.
Don’t use patches on wounded, inflamed or other uncomfortable skin part.
Store product avoiding hot/cold place and direct sunlight.
Keep out of reach of children.

KEEP OUT OF REACH OF CHILDREN

Uses

Helps improve wrinkle problem
Improves moisturizing and elasticity

Directions

1) Before sleep, cleanse your face and remove water.
2) Open the pouch and plastic case carefully.
3) Be careful not to touch the center area with fingers and remove white protective film.
4) Attach patches on the area you want and press vertically with fingers for about 1 minute.
5) Peel softly in next morning. (or after 2 hours minimum)